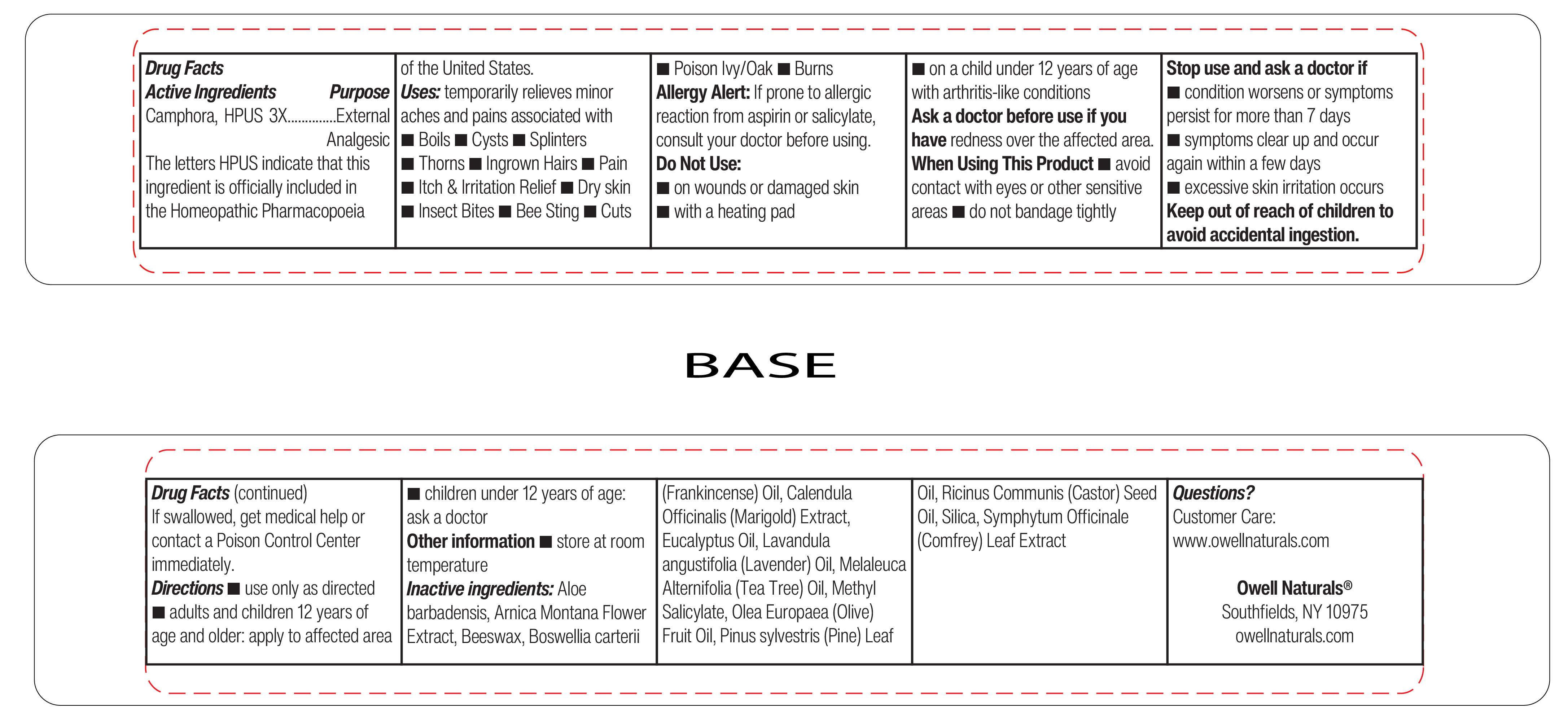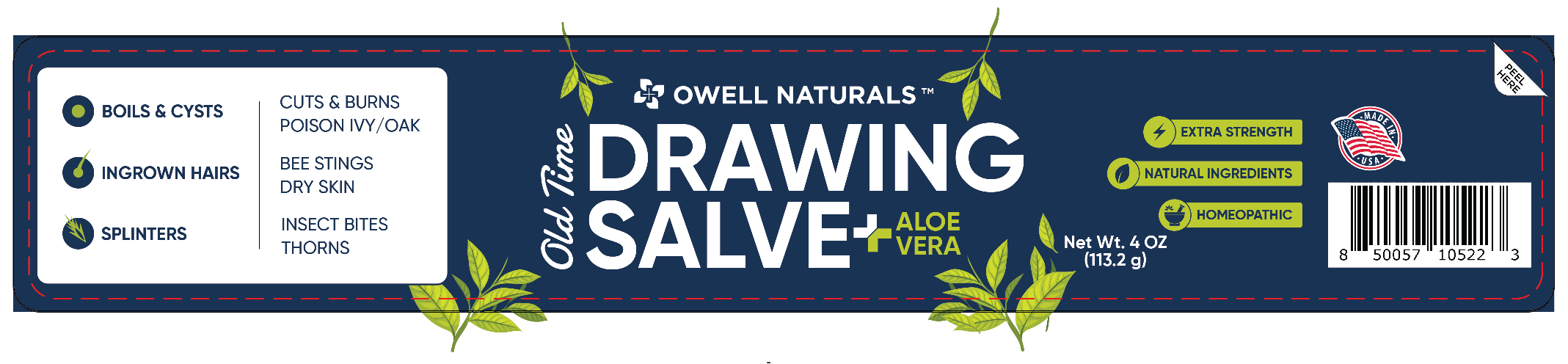 DRUG LABEL: OLD TIME Owell Naturals Draw Salve with Aloe
NDC: 83570-560 | Form: SALVE
Manufacturer: Owell Naturals Brand LLC
Category: homeopathic | Type: HUMAN OTC DRUG LABEL
Date: 20250912

ACTIVE INGREDIENTS: CAMPHOR (NATURAL) 2.26 g/113.2 g
INACTIVE INGREDIENTS: WHITE WAX; CALENDULA OFFICINALIS FLOWER; ARNICA MONTANA FLOWER; LAVENDER OIL; TEA TREE OIL; WHITE PINE OIL; EUCALYPTUS OIL; OLIVE OIL; CASTOR OIL; FRANKINCENSE OIL; COMFREY LEAF; METHYL SALICYLATE; STELLARIA MEDIA; ALOE VERA LEAF

Owell Naturals Draw Salve with Aloe

ACTIVE INGREDIENT

Camphora, HPUS 3X

Uses

temporarily relieves minor aches and pains associated with

Boils

Cysts

Splinters

Thorns

Ingrown Hairs

Pain

Itch & Irritation Relief

Dry Skin

Insect Bites

Bee Sting

Cuts

Poison Ivy/Oak

Burns

Do not Use

on wounds or damaged skin

with a heating pad

on a child under 12 years of age with arthritis-like conditions

Ask a doctor before use if you have

redness over the affected area

When using this product

avoid contact with eyes or other sensitive areas

do not bandage tightly

Stop use and ask a doctor if

condition worsens or symptoms persist for more than 7 days

symptoms clear up and occur again within a few days

excessive skin irritation occurs

Keep out of reach of children to avoid accidental ingestion.

If swallowed, get medical help or contact a Poison Control Center immediately.

Directions

Use only as directed

adults and children 12 years of age and older, apply to affected area

children under 12 years of age, ask a doctor

OTHER SAFETY INFORMATION

store at room temperature

QUESTIONS

Manufactured for Owell Naturals

Southfields, NY 10975

owellnaturals.com

Questions?

Customer Care: www.owellnaturals.com

Inactive Ingredients

Aloe barbadensis (Aloe Vera), Arnica Montana Flower Extract, Beeswax, Boswellia carterii (Frankincense) Oil, Calendula Officinalis (Marigold) Extract, Eucalyptus Oil,

Lavandula angustifolia (Lavender) Oil, Melaleuca alternifolia (Tea Tree) Oil, Methyl Salicylate, Olea Europaea (Olive) Fruit Oil,

Pinus sylvestris (Pine) Leaf Oil, Ricinus communis (Castor) Seed Oil, Silica, Symphytum Officinale (Comfrey) Leaf Extract

PURPOSE

Arnica Montana HPUS 30C 1 percent Purpose Anti-inflammatory

Silicea HPUS 30C 0.10 percent Purpose Minor skin eruptions

Allergy Alert: If prone to allergic reaction from aspirin or salicylate, consult your doctor before using.

Do Not Use:

on wounds or damaged skin

with a heating pad

on a child under 12 years of age with arthritis-like conditions

Stop use and ask a doctor if

condition worsens or symptoms persist for more than 7 days

symptoms clear up and occur again within a few days

PACKAGE LABEL

ON DRAW SALVE WITH ALOE VERA 4.OZ.